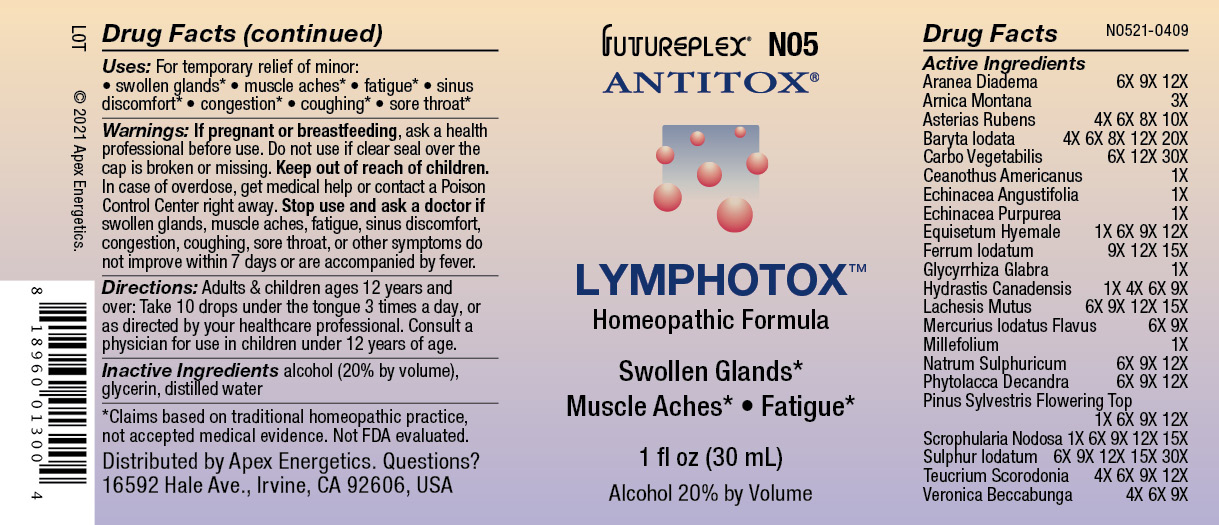 DRUG LABEL: N05
NDC: 63479-1405 | Form: SOLUTION/ DROPS
Manufacturer: Apex Energetics Inc.
Category: homeopathic | Type: HUMAN OTC DRUG LABEL
Date: 20240108

ACTIVE INGREDIENTS: BARIUM IODIDE 20 [hp_X]/1 mL; MERCUROUS IODIDE 9 [hp_X]/1 mL; ACHILLEA MILLEFOLIUM 1 [hp_X]/1 mL; SODIUM SULFATE 12 [hp_X]/1 mL; PHYTOLACCA AMERICANA ROOT 12 [hp_X]/1 mL; SCROPHULARIA NODOSA 15 [hp_X]/1 mL; SULFUR IODIDE 30 [hp_X]/1 mL; TEUCRIUM SCORODONIA FLOWERING TOP 12 [hp_X]/1 mL; VERONICA BECCABUNGA 9 [hp_X]/1 mL; ACTIVATED CHARCOAL 30 [hp_X]/1 mL; ECHINACEA ANGUSTIFOLIA 1 [hp_X]/1 mL; ECHINACEA PURPUREA 1 [hp_X]/1 mL; EQUISETUM HYEMALE 12 [hp_X]/1 mL; FERROUS IODIDE 15 [hp_X]/1 mL; PINUS SYLVESTRIS FLOWERING TOP 12 [hp_X]/1 mL; ARANEUS DIADEMATUS 12 [hp_X]/1 mL; ARNICA MONTANA 3 [hp_X]/1 mL; GLYCYRRHIZA GLABRA 1 [hp_X]/1 mL; GOLDENSEAL 9 [hp_X]/1 mL; LACHESIS MUTA VENOM 15 [hp_X]/1 mL; ASTERIAS RUBENS 10 [hp_X]/1 mL; CEANOTHUS AMERICANUS LEAF 1 [hp_X]/1 mL
INACTIVE INGREDIENTS: ALCOHOL; GLYCERIN; WATER

N05

Active Ingredients
Aranea Diadema | 6X 9X 12X
Arnica Montana | 3X
Asterias Rubens | 4X 6X 8X 10X
Baryta Iodata | 4X 6X 8X 12X 20X
Carbo Vegetabilis | 6X 12X 30X
Ceanothus Americanus | 1X
Echinacea Angustifolia | 1X
Echinacea Purpurea | 1X
Equisetum Hyemale | 1X 6X 9X 12X
Ferrum Iodatum | 9X 12X 15X
Glycyrrhiza Glabra | 1X
Hydrastis Canadensis | 1X 4X 6X 9X
Lachesis Mutus | 6X 9X 12X 15X
Mercurius Iodatus Flavus | 6X 9X
Millefolium | 1X
Natrum Sulphuricum | 6X 9X 12X
Phytolacca Decandra | 6X 9X 12X
Pinus Sylvestris Flowering Top | 1X 6X 9X 12X
Scrophularia Nodosa | 1X 6X 9X 12X 15X
Sulphur Iodatum | 6X 9X 12X 15X 30X
Teucrium Scorodonia | 4X 6X 9X 12X
Veronica Beccabunga | 4X 6X 9X

INDICATIONS AND USAGE

For temporary relief of minor:

swollen glands*

muscle aches*

fatigue*

sinus discomfort*

congestion*

coughing*

sore throat*

*Claims based on traditional homeopathic practice, not accepted medical evidence. Not FDA evaluated.

PURPOSE

Uses: For temporary relief of minor:

swollen glands*

muscle aches*

fatigue*

sinus discomfort*

congestion*

coughing*

sore throat*

*Claims based on traditional homeopathic practice, not accepted medical evidence. Not FDA evaluated.

WARNINGS

If pregnant or breastfeeding, ask a health professional before use.

Do not use if clear seal over the cap is broken or missing.

PREGNANCY OR BREAST FEEDING

If pregnant or breastfeeding, ask a health professional before use.

Do not use if clear seal over the cap is broken or missing.

Keep out of reach of children. In case of overdose, get medical help or contact a Poison Control Center right away.

Stop use and ask a doctor if swollen glands, muscle aches, fatigue, sinus discomfort, congestion, coughing, sore throat, or other symptoms do not improve within 7 days or are accompanied by fever.

DOSAGE AND ADMINISTRATION

Adults & children ages 12 years and over: Take 10 drops under the tongue 3 times a day, or as directed by your healthcare professional. Consult a physician for use in children under 12 years of age.

Inactive Ingredients

alcohol (20% by volume), glycerin, distilled water

Distributed by Apex Energetics. Questions?

16592 Hale Ave., Irvine, CA 92606, USA

PACKAGE LABEL

FUTUREPLEX® N05

ANTITOX®

LYMPHOTOX™

Homeopathic Formula

Swollen Glands*

Muscle Aches*

Fatigue*

1 fl oz (30 mL)

Alcohol 20% by Volume